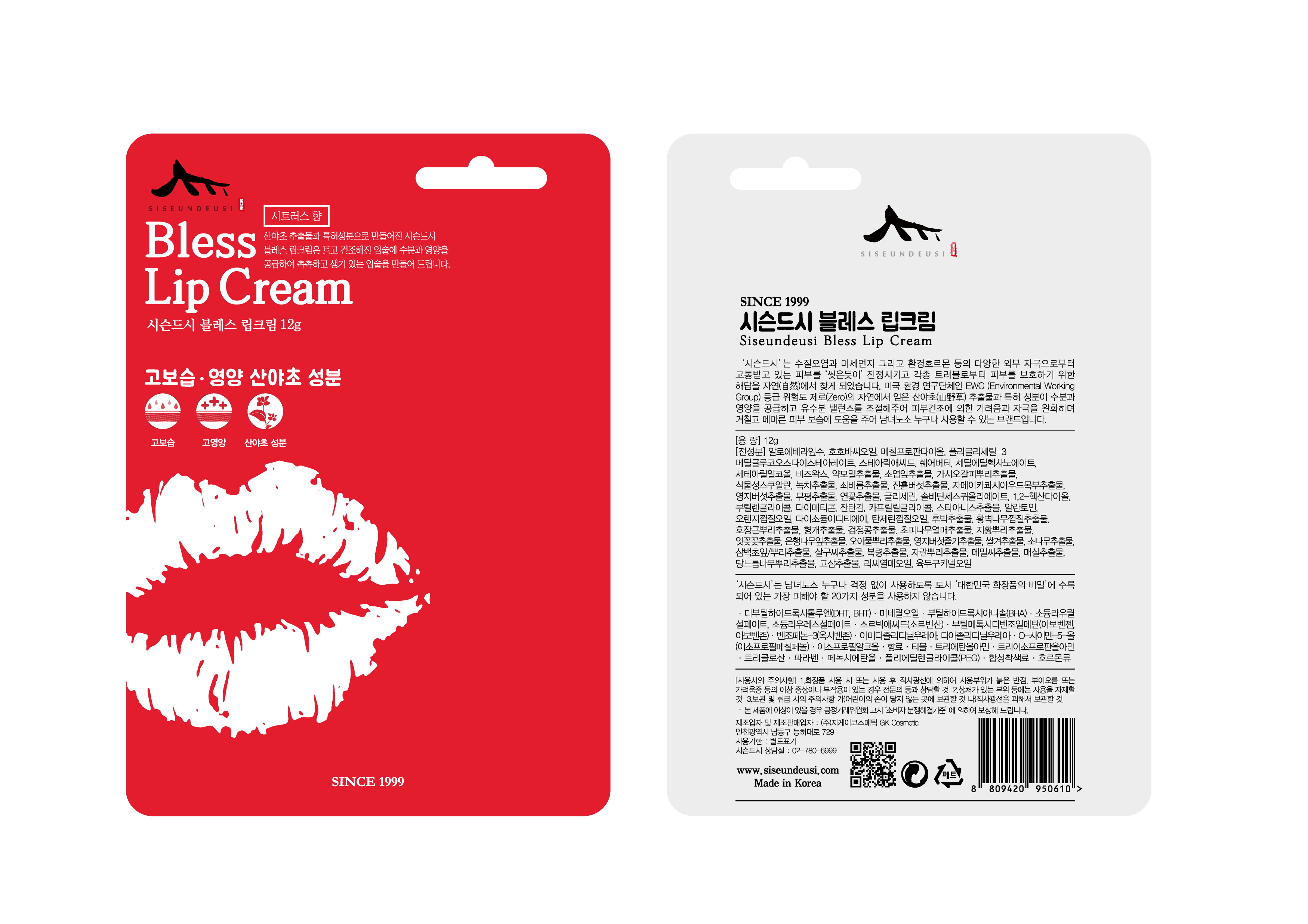 DRUG LABEL: SISEUNDEUSI  BLESS LIP
NDC: 70098-0014 | Form: CREAM
Manufacturer: GK COSMETIC CO., LTD.
Category: otc | Type: HUMAN OTC DRUG LABEL
Date: 20180209

ACTIVE INGREDIENTS: GLYCERIN 2 g/100 g
INACTIVE INGREDIENTS: BUTYLENE GLYCOL; ALLANTOIN

Drug Facts

ACTIVE INGREDIENT

glycerin

INACTIVE INGREDIENT

houttuynia cordata extract, butylene glycol,etc

PURPOSE

relieving skin troubles

keep out of reach of the children

INDICATIONS AND USAGE

Apply gentle amount of lip cream smoothly on your lip surroundings

WARNINGS

1. Do not use in the following cases (Eczema and scalp wounds)
2.Side Effects
1)Due to the use of this druf if rash, irritation, itching and symptopms of hypersnesitivity occur dicontinue use and consult your phamacisr or doctor
3.General Precautions
1)If in contact with the eyes, wash out thoroughty with water If the symptoms are servere, seek medical advice immediately
2)This product is for exeternal use only. Do not use for internal use
4.Storage and handling precautions
1)If possible, avoid direct sunlight and store in cool and area of low humidity
2)In order to maintain the quality of the product and avoid misuse
3)Avoid placing the product near fire and store out in reach of children

DOSAGE AND ADMINISTRATION

for external use only